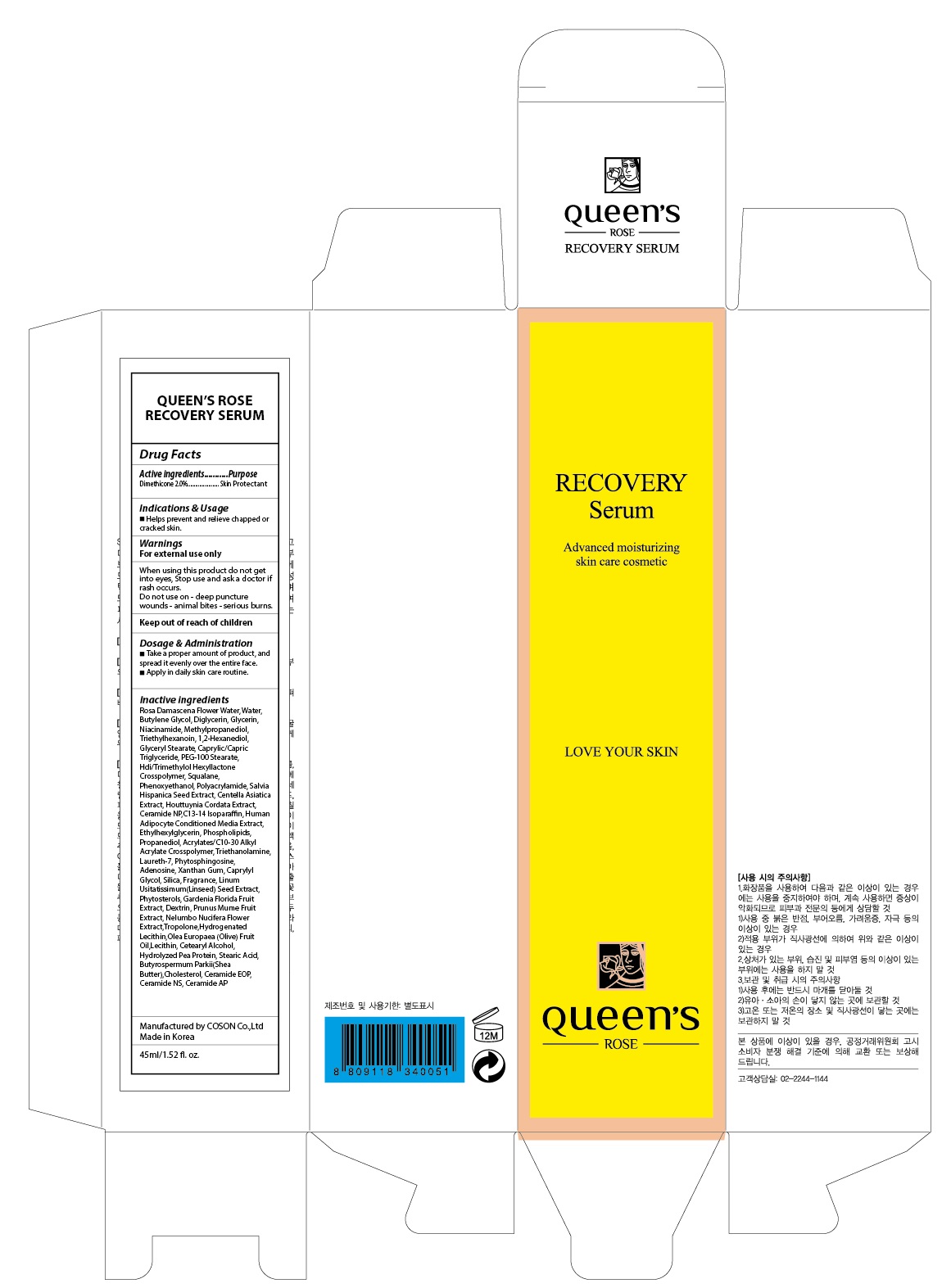 DRUG LABEL: QUEENS ROSE RECOVERY SERUM
NDC: 71252-030 | Form: LIQUID
Manufacturer: Cdpharmtec Co.,ltd
Category: otc | Type: HUMAN OTC DRUG LABEL
Date: 20170324

ACTIVE INGREDIENTS: Dimethicone 0.9 g/45 mL
INACTIVE INGREDIENTS: ROSA DAMASCENA FLOWER OIL; Water

ACTIVE INGREDIENT

Active ingredients: Dimethicone 2.0%

INACTIVE INGREDIENT

Inactive ingredients: Rosa Damascena Flower Water, Water, Butylene Glycol, Diglycerin, Glycerin, Niacinamide, Methylpropanediol, Triethylhexanoin, 1,2-Hexanediol, Glyceryl Stearate, Caprylic/Capric Triglyceride, PEG-100 Stearate, Hdi/Trimethylol Hexyllactone Crosspolymer, Squalane, Phenoxyethanol, Polyacrylamide, Salvia Hispanica Seed Extract, Centella Asiatica Extract, Houttuynia Cordata Extract, Ceramide NP,C13-14 Isoparaffin, Human Adipocyte Conditioned Media Extract, Ethylhexylglycerin, Phospholipids, Propanediol, Acrylates/C10-30 Alkyl Acrylate Crosspolymer, Triethanolamine, Laureth-7, Phytosphingosine, Adenosine, Xanthan Gum, Caprylyl Glycol, Silica, Fragrance, Linum Usitatissimum(Linseed) Seed Extract, Phytosterols, Gardenia Florida Fruit Extract, Dextrin, Prunus Mume Fruit Extract, Nelumbo Nucifera Flower Extract,Tropolone,Hydrogenated Lecithin,Olea Europaea (Olive) Fruit Oil,Lecithin, Cetearyl Alcohol, Hydrolyzed Pea Protein, Stearic Acid, Butyrospermum Parkii(Shea Butter),Cholesterol, Ceramide EOP, Ceramide NS, Ceramide AP

PURPOSE

Purpose: Skin Protectant

WARNINGS

Warnings: When using this product do not get into eyes, Stop use and ask a doctor if rash occurs. Do not use on - deep puncture wounds - animal bites - serious burns.

KEEP OUT OF REACH OF CHILDREN

INDICATIONS & USAGE

Indications & Usage: Helps prevent and relieve chapped or cracked skin.

DOSAGE & ADMINISTRATION

Dosage & Administration: - Take a proper amount of product, and spread it evenly over the entire face. - Apply in daily skin care routine.